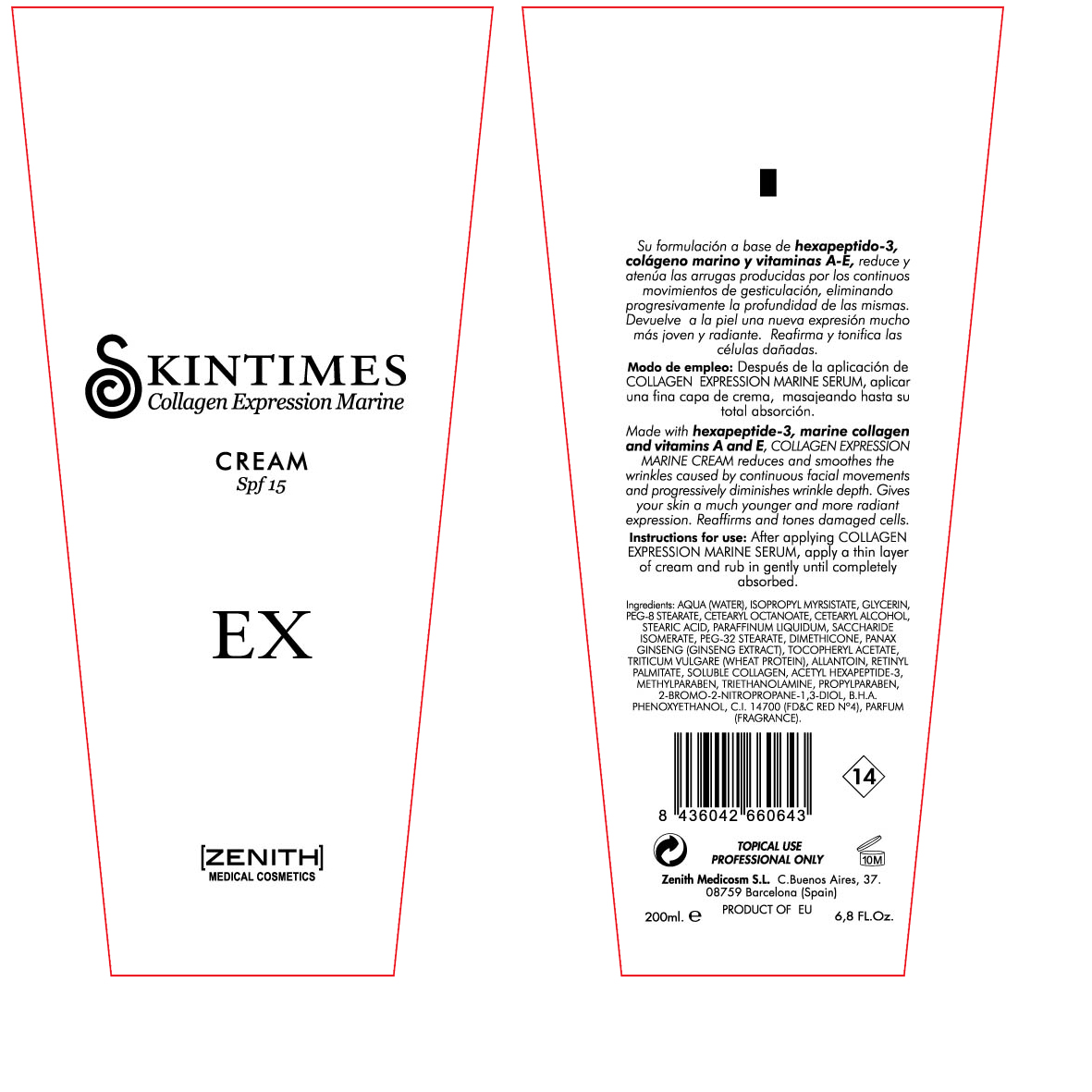 DRUG LABEL: Expression
NDC: 42248-115 | Form: CREAM
Manufacturer: Zenith Medicosm SL
Category: otc | Type: HUMAN OTC DRUG LABEL
Date: 20120121

ACTIVE INGREDIENTS: OCTINOXATE 15 mL/200 mL
INACTIVE INGREDIENTS: ISOPROPYL MYRISTATE; PROPYLPARABEN; ALPHA-TOCOPHEROL ACETATE; DIMETHICONE; GLYCERIN; CETEARYL ETHYLHEXANOATE; WATER; MINERAL OIL; CETOSTEARYL ALCOHOL; PEG-8 STEARATE; TROLAMINE; SACCHARIDE ISOMERATE; WHEAT GERM; ACETYL HEXAPEPTIDE-3; BRONOPOL; BUTYLATED HYDROXYANISOLE; PHENOXYETHANOL; ALLANTOIN; VITAMIN A PALMITATE; FD&C RED NO. 4; COLLAGEN, SOLUBLE, FISH SKIN

Drug Facts

Active Ingredient

Octinoxate 7.5%

Description

Made with hexapeptides-3, marine collagen and vitamins A and E, COLLAGEN EXPRESSION MARINE CREAM reduces and smoothes the wrinkles caused by continuous facial movements and progressively diminishes wrinkle depth. Gives skin a much younger and more radiant expression. Reaffirms and tones damaged cells.

200ml. 6.8Fl.Oz

Warning

TOPICAL USE

PROFESSIONAL ONLY

Instructions For Use:

After applying COLLAGEN EXPRESSION MARINE SERUM, apply a thin layer of cream and rub in gently until completely absorbed.